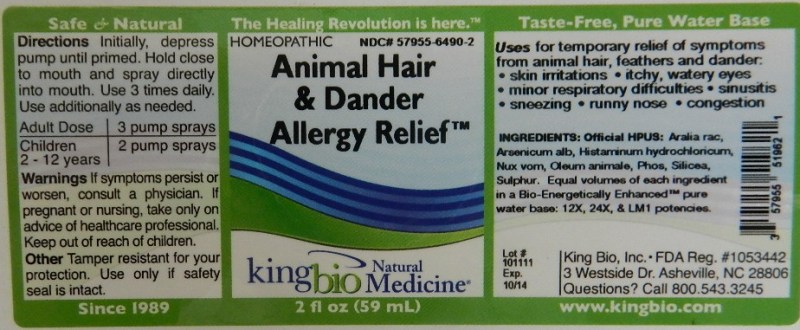 DRUG LABEL: Animal Hair and Dander Allergy Relief
NDC: 57955-6490 | Form: LIQUID
Manufacturer: King Bio Inc.
Category: homeopathic | Type: HUMAN OTC DRUG LABEL
Date: 20111123

ACTIVE INGREDIENTS: ARALIA RACEMOSA ROOT 12 [hp_X]/59 mL; ARSENIC TRIOXIDE 12 [hp_X]/59 mL; HISTAMINE DIHYDROCHLORIDE 12 [hp_X]/59 mL; STRYCHNOS NUX-VOMICA SEED 12 [hp_X]/59 mL; CERVUS ELAPHUS HORN OIL 12 [hp_X]/59 mL; PHOSPHORUS 12 [hp_X]/59 mL; SILICON DIOXIDE 12 [hp_X]/59 mL; SULFUR 12 [hp_X]/59 mL
INACTIVE INGREDIENTS: WATER

Animal Hair and Dander Allergy Relief

Active Ingredients

Official HPUS: Aralia Racemosa, Arsenicum Album, Histaminum Hydrochloricum, Nux Vomica, Oleum Animale, Phosphorus, Silicea and Sulphur.

Reference image animal hair.jpg

Inactive Ingredient

Equal volumes of each ingredient in a Bio-Energetically Enhanced pure water base; 12X, 24X, LM1 potencies.

Reference image animal hair.jpg

Dosage and Administration

Directions Initially, depress pump until primed. Hold close to mouth and spray directly into mouth. Use 3 times daily. Use additionally as needed.

Adult Dose 3 pump sprays

Children (2-12 years) 2 pump sprays

Reference image animal hair.jpg

Warnings

If symptoms persist or worsen, consult a physician. If pregnant or nursing, take only on advice of healthcare professional. Keep out of reach of children.

Other Tamper resistant for your protection. Use only if safety seal is intact.

Reference image animal hair.jpg

Keep out of reach of children.

Reference image animal hair.jpg

Indications and Usage

Uses for temporary relief of symptoms from animal hair, feathers and dander

- skin irritations
- itchy, watery eyes
- minor respiratory difficulties
- sinusitis
- sneezing
- runny nose
- congestion

Reference image animal hair.jpg

Purpose

Uses for temporary relief of symptooms from animal hair, feathers and dander, Skin irritations, itchy, watery eyes, minor respiratory difficulties, sinusitis, sneezing, runny nose and congestion.

Reference image animal hair.jpg

PACKAGE LABEL

King Bio Inc,

3 Westside Drive

Asheville, NC 28806

Questions? Call 800.543.3245

www.kingbio.com